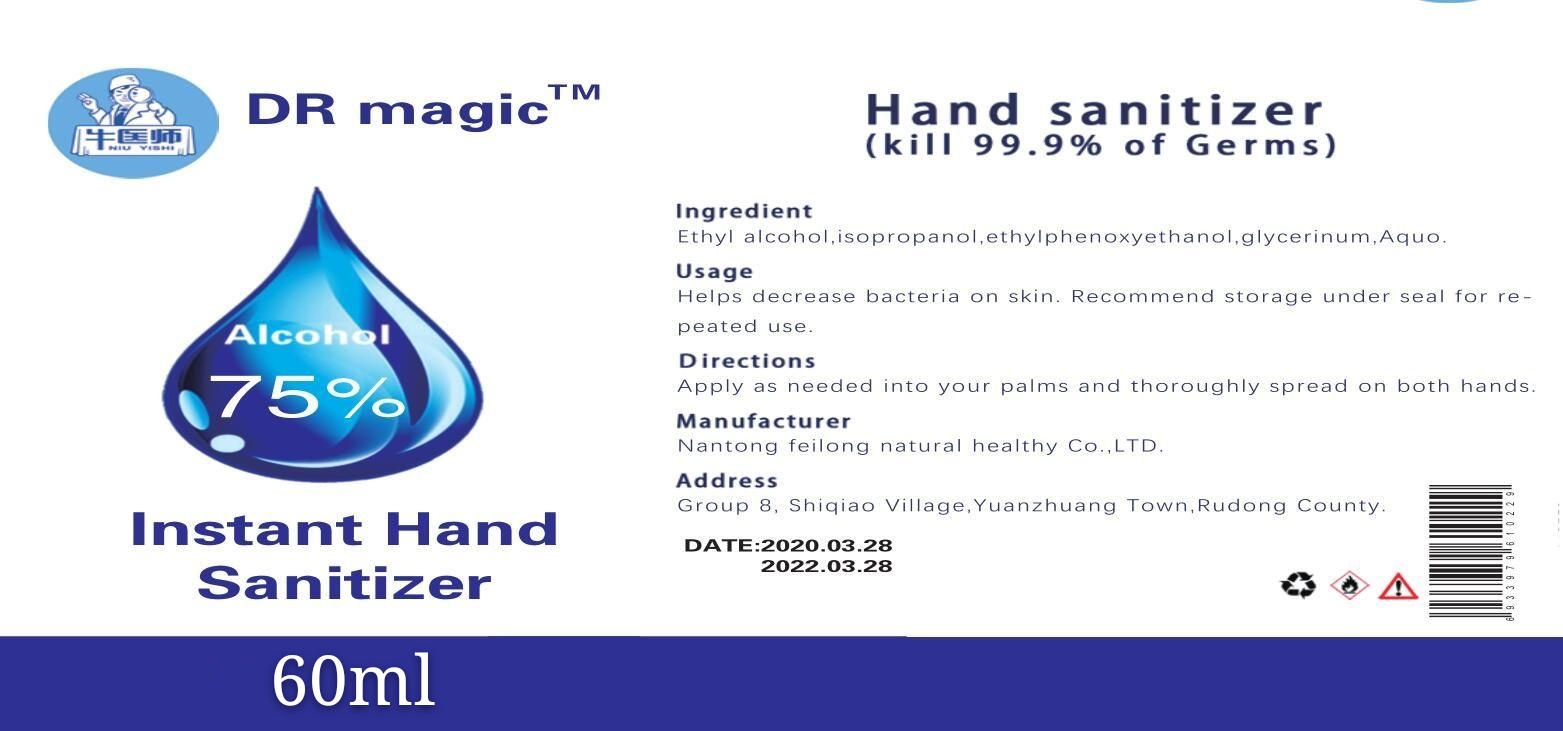 DRUG LABEL: Instant hand sanitizer
NDC: 55447-006 | Form: LIQUID
Manufacturer: Nan tong Feilong Natural Healthy Co.,LTD
Category: otc | Type: HUMAN OTC DRUG LABEL
Date: 20200730

ACTIVE INGREDIENTS: ALCOHOL 45 mL/60 mL
INACTIVE INGREDIENTS: 2-(2-ETHYLHEXYLOXY)ETHANOL; GLYCERIN; ISOPROPYL ALCOHOL; WATER

Active Ingredient(s)

Isopropyl Alcohol 75% v/v. Purpose: Antiseptic

Purpose

Disinfection
Sterilization
No Rinseing

INDICATIONS & USAGE

Helps decrease bacteria on skin. Recommend storage under seal for repeated use

Warnings

For external use only. Flammable. Keep away from heat or flame

Keep out of reach of children. If swallowed, get medical help or contact a Poison Control Center right away.

Directions

- Place enough product on hands to cover all surfaces. Rub hands together until dry.
- Supervise children under 6 years of age when using this product to avoid swallowing.

Inactive ingredients

iso propanol,ethylphenoxyethanol,glycerinum,Aquo